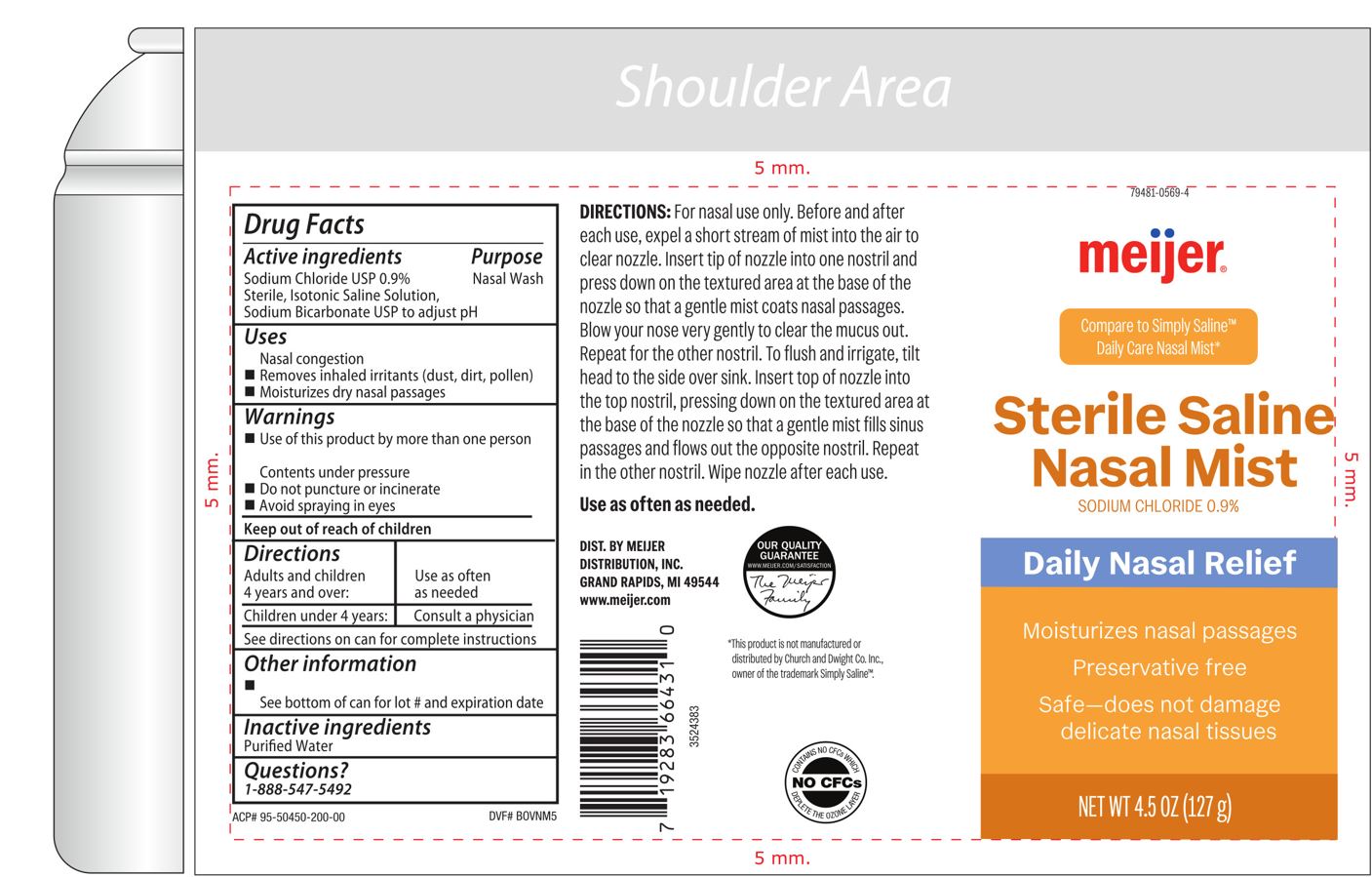 DRUG LABEL: Sterile Saline Mist
NDC: 79481-0569 | Form: SPRAY
Manufacturer: Meijer, Inc.
Category: otc | Type: HUMAN OTC DRUG LABEL
Date: 20251201

ACTIVE INGREDIENTS: SODIUM CHLORIDE 0.9 g/100 g
INACTIVE INGREDIENTS: WATER

Sterile Nasal Saline Mist

Active Ingredient

Sodium Chloride .9%

Sterile, Hypertonic Saline Solution,

Sodium Bicarbonate to adjust pH

Purpose

Nasal Wash

Uses

- Nasal congestion
- Removes inhaled irritants (dust, dirt, pollen)
- Moisturizes dry nasal passages

Directions

Adults and children 4 years and over: Use as often as needed
Children under 4 years: Consult a physician
See directions on can for complere instructions

For nasal use only.

Before use, expel a short stream of mist into the air. Insert tip of nozzle into one nostril and press down on the textured area at the base of the nozzle so that a gentle mist coats nasal passages. Blow your nose very gently to clear the mucus out. Repeat for the other nostriil.

To flush and irrigate, tilt head to the side over sink. Insert top of nozzle into the top nostril, pressing down on the textured area at the base of the nozzle so that a gentle mist fills sinus passages and flows out the opposite nostril. Repeat in other nostril.

Wipe nozzle after each use.

Warnings

Use of this product by more than one person may spread infection
Contents under pressure
Do not puncture or incinerate
Avoid spraying in eyes

Other Information

Store between 59 and 86 degree F

Inactive ingredients

Purfied Water

QUESTIONS ?

1-888-547-5492